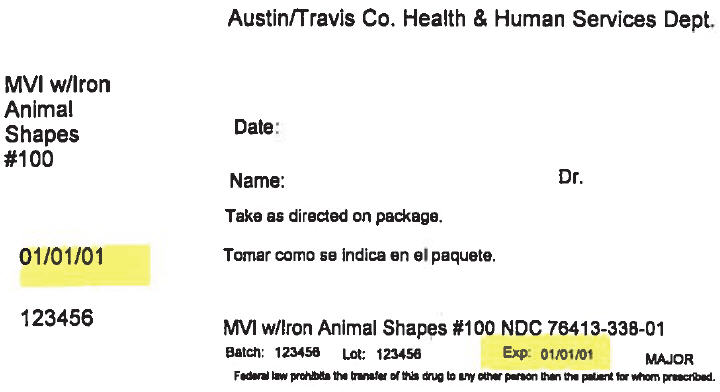 DRUG LABEL: Animal Shapes w/Iron Chewtabs
NDC: 76413-338 | Form: TABLET, CHEWABLE
Manufacturer: Central Texas Community Health Centers
Category: other | Type: DIETARY SUPPLEMENT
Date: 20170918

ACTIVE INGREDIENTS: Vitamin A 2500 [iU]/1 1; Ascorbic Acid 60 mg/1 1; Cholecalciferol 400 [iU]/1 1; .Alpha.-Tocopherol Acetate, dl- 15 [iU]/1 1; Thiamine Mononitrate 1.05 mg/1 1; Riboflavin 1.2 mg/1 1; Niacinamide 13.5 mg/1 1; Pyridoxine 1.05 mg/1 1; Folic acid 300 ug/1 1; Cyanocobalamin 4.5 ug/1 1; Ferrous fumarate 15 mg/1 1
INACTIVE INGREDIENTS: Sucrose; Dextrose, Unspecified Form; Stearic acid; Gelatin, Unspecified; magnesium stearate; anhydrous dibasic calcium phosphate; silicon dioxide; FD&C Red No. 40; Aluminum Oxide; FD&C Yellow No. 6; sodium ascorbate; FD&C Blue No. 2; Tocopherol; Sodium Benzoate; Sorbic acid; Butylated Hydroxytoluene

Animal SHAPES with iron

STATEMENT OF IDENTITY

Supplement Facts
Serving Size: | ½ Tablet (2-3 years of age)
 | 1 Tablet (4 years of age & older)
Amount Per Tablet |  |  | %DV [% Daily Value (DV) for Children 2-3 years of age (½ tablet).] | %DV [%Daily Value (DV) for Adults and Children 4 or more years of age (1 tablet).]
Vitamin A (as Acetate & Beta Carotene) |  | 3,000 I.U. | 60% | 60%
Vitamin C (as Sodium Ascorbate) |  | 60 mg. | 75% | 100%
Vitamin D-3 (as Cholecalciferol) |  | 600 I.U. | 75% | 150%
Vitamin E (as dl-Alpha Tocopheryl Acetate) |  | 30 I.U. | 150% | 100%
Vitamin K (as Phytonadione) |  | 55 mcg. | [% Daily Value (DV) not established.] | 69%
Vitamin B-1 (as Thiamine Mononitrate) |  | 1.5 mg. | 107% | 100%
Vitamin B-2 (Riboflavin) |  | 1.7 mg. | 106% | 100%
Niacinamide (Vitamin B-3) |  | 15 mg. | 83% | 75%
Vitamin B-6 (as Pyridoxine HCl) |  | 2 mg. | 143% | 100%
Folic Acid |  | 0.4 mg. | 100% | 100%
Vitamin B-12 (as Cyanocobalamin) |  | 6 mcg. | 100% | 100%
Biotin |  | 40 mcg. | 13% | 13%
Pantothenic Acid (as Calcium Pantothenate) |  | 10 mg. | 100% | 100%
Calcium (as Calcium Carbonate) |  | 100 mg. | 6% | 10%
Iron (as Ferrous Fumarate) |  | 18 mg. | 90% | 100%
Iodine (as Potassium Iodide) |  | 150 mcg. | 107% | 100%
Zinc (as Zinc Oxide) |  | 12 mg. | 75% | 80%
Copper (as Cupric Oxide) |  | 2 mg. | 100% | 100%
Sodium (as Sodium Ascorbate) |  | 21 mg. |  | <1%

OTHER INGREDIENTS: Sorbitol, Sugar, Gelatin, Citric Acid, Stearic Acid, Starch, Cherry Flavor, Orange Flavor, Grape Flavor, Silica, Mannitol, Dicalcium Phosphate, Maltodextrin, Microcrystalline Cellulose, Magnesium Stearate, FD&C Red #40 Lake, FD&C Yellow #6 Lake, Sodium Ascorbate, FD&C Blue #2 Lake, Triglycerides, Tocopherols, Sodium Benzoate, Sorbic Acid, Tricalcium Phosphate, Ascorbyl Palmitate and BHT. Cherry flavor contains: Modified Corn Starch Grape flavor contains: Maltodextrin, Modified Corn Starch and Silica Orange flavor contains: Maltodextrin, Lactose [Contains: Milk] , Natural Flavoring, Modified Corn Starch and Sugar

DIRECTIONS

Adults and children 4 years of age and older, chew one (1) tablet daily, preferably with a meal. For children, 2-3 years of age, chew one-half (1/2) tablet daily. As a reminder, discuss the supplements and medications you take with your health care providers.

WARNING

If you are pregnant, nursing, taking any medications or planning any medical procedure, consult your doctor before use. Discontinue use and consult your doctor if any adverse reactions occur. THIS PRODUCT IS INTENDED FOR USE BY CHILDREN UNDER ADULT SUPERVISION.

WARNING: Accidental overdose of iron-containing products is a leading cause of fatal poisoning in children under six. KEEP THIS PRODUCT OUT OF THE REACH OF CHILDREN. In case of accidental overdose, call a doctor or Poison Control Center immediately.

SAFE HANDLING WARNING

KEEP OUT OF THE REACH OF CHILDREN. STORE IN A DRY PLACE AND AVOID EXCESSIVE HEAT. TAMPER RESISTANT: DO NOT USE IF SEAL UNDER CAP IS BROKEN OR MISSING.

HEALTH CLAIM

‡This product is not manufactured or distributed by Bayer, owner of the registered trademark Flintstones™ Complete.

Distributed by: MAJOR® PHARMACEUTICALS
31778 Enterprise Drive, Livonia, MI 48150, USA
Questions or Comments? (800) 616-2471

M-29
10861-07-16
Rev. 07/16

PRINCIPAL DISPLAY PANEL - 100 Tablet Bottle Label

Austin/Travis Co. Health & Human Services Dept.

MVI w/Iron
Animal
Shapes
#100

Date:

Name:
Dr.

Take as directed on package.

01/01/01

123456

MVI w/Iron Animal Shapes #100 NDC 76413-338-01

Batch:
123456
Lot:
123456
Exp:
01/01/01

MAJOR

Federal law prohibits the transfer of this drug to any other person than the patient for whom prescribed.